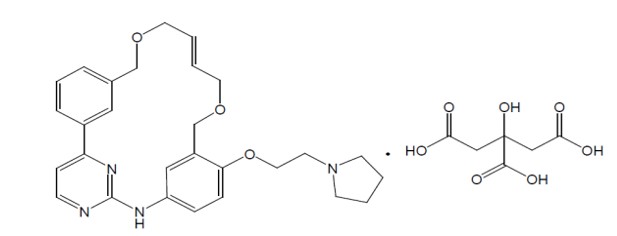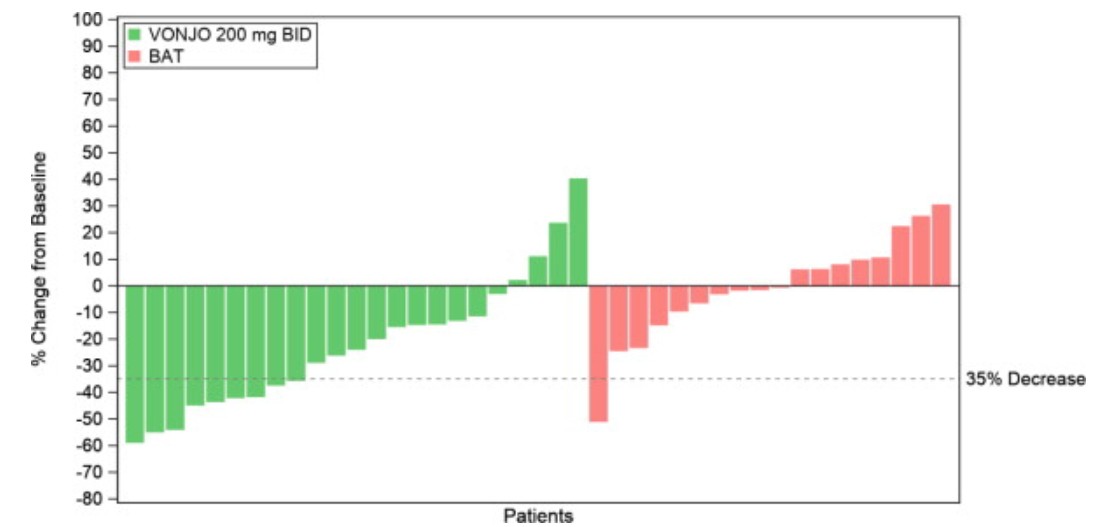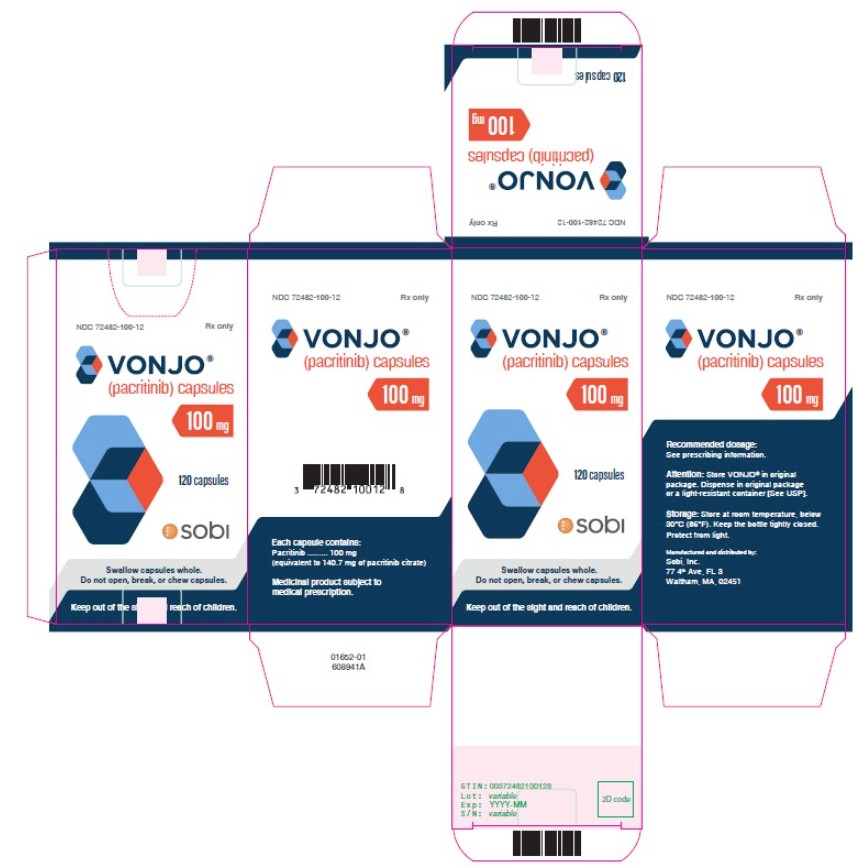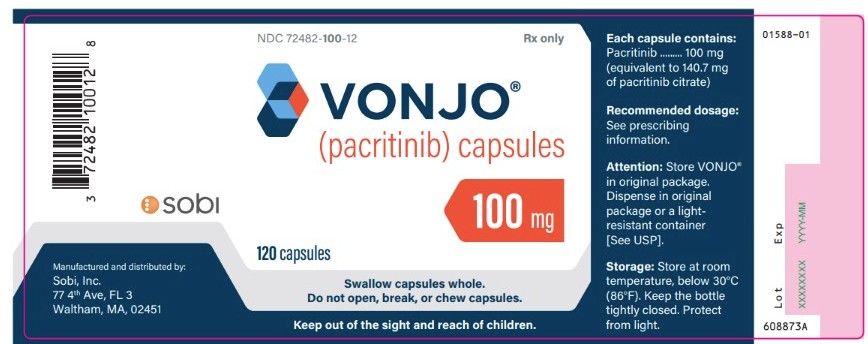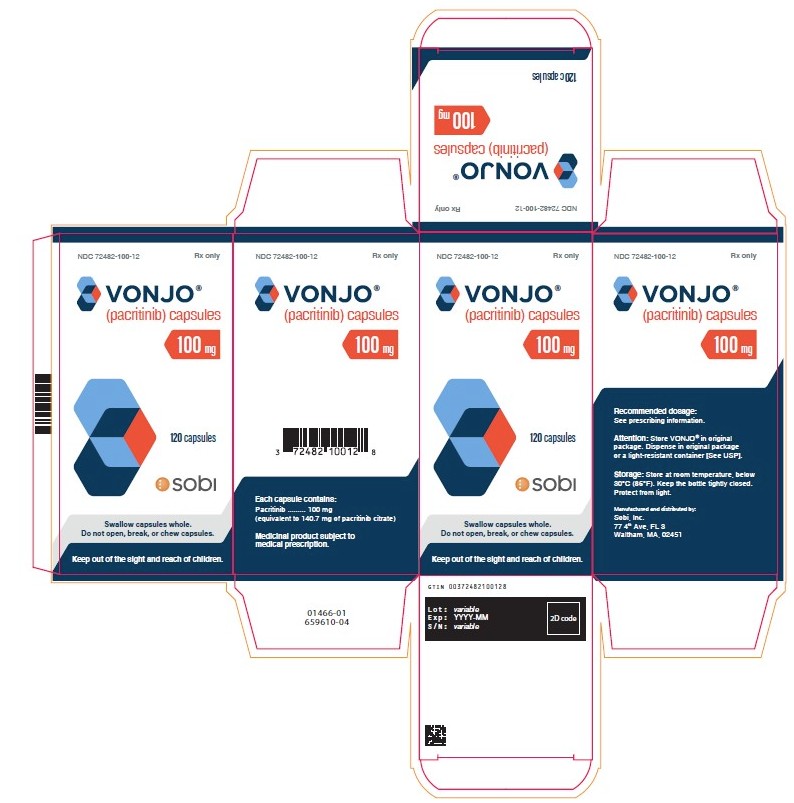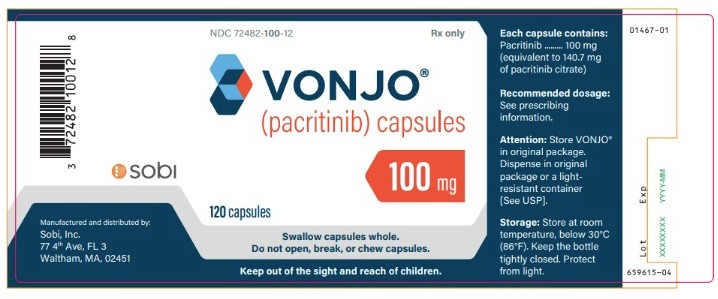 DRUG LABEL: Vonjo
NDC: 72482-100 | Form: CAPSULE
Manufacturer: Sobi, Inc.
Category: prescription | Type: HUMAN PRESCRIPTION DRUG LABEL
Date: 20251010

ACTIVE INGREDIENTS: PACRITINIB 100 mg/1 1
INACTIVE INGREDIENTS: MICROCRYSTALLINE CELLULOSE; POLYETHYLENE GLYCOL 8000; MAGNESIUM STEARATE; GELATIN, UNSPECIFIED

HIGHLIGHTS OF PRESCRIBING INFORMATION

These highlights do not include all the information needed to use VONJO safely and effectively. See full prescribing information for VONJO.
VONJO®(pacritinib) capsules, for oral use
Initial U.S. Approval: 2022

RECENT MAJOR CHANGES

Warnings and Precautions (5.9) 11/2024

Warnings and Precautions (5.2) 08/2025

Dosage and Administration (2.6) 10/2025

1 INDICATIONS AND USAGE

VONJO is a kinase inhibitor indicated for the treatment of adults with intermediate or high-risk primary or secondary (post-polycythemia vera or post-essential thrombocythemia) myelofibrosis with a platelet count below 50 × 10 ^9/L (1).

This indication is approved under accelerated approval based on spleen volume reduction. Continued approval for this indication may be contingent upon verification and description of clinical benefit in a confirmatory trial(s).

2 DOSAGE AND ADMINISTRATION

- Recommended dosage is 200 mg orally twice daily (2.1).
- May be taken with or without food (2.1).

3 DOSAGE FORMS AND STRENGTHS

Capsules: 100 mg (3)

4 CONTRAINDICATIONS

Concomitant use of strong CYP3A4 inhibitors or inducers (4)

5 WARNINGS AND PRECAUTIONS

- Hemorrhage: Avoid use in patients with active bleeding and hold VONJO prior to any planned surgical procedures. May require dose interruption, dose reduction or permanent discontinuation depending on severity (5.1).
- Diarrhea: Manage significant diarrhea with anti-diarrheals, dose reduction, or dose interruption (5.2).
- Thrombocytopenia: Manage by dose reduction or interruption (5.3).
- Prolonged QT Interval: Avoid use in patients with baseline QTc >480 msec. Interrupt and reduce VONJO dosage in patients who have a QTcF >500 msec. Correct hypokalemia prior to and during VONJO administration (5.4).
- Major Adverse Cardiac Events (MACE): Risk may be increased in current/past smokers and patients with other cardiovascular risk factors. Monitor for signs, evaluate and treat promptly (5.5).
- Thrombosis: Including deep venous thrombosis, pulmonary embolism, and arterial thrombosis may occur. Monitor for signs, evaluate and treat promptly (5.6).
- Secondary Malignancies: Lymphoma and other malignancies may occur. Past/current smokers may be at increased risk (5.7).
- Risk of Infection: Delay starting VONJO until active serious infections have resolved. Observe for signs and symptoms of infection and manage promptly (5.8).

6 ADVERSE REACTIONS

The most common (≥20% of patients) adverse reactions are diarrhea, thrombocytopenia, nausea, anemia, and peripheral edema (6.1).

To report SUSPECTED ADVERSE REACTIONS, contact Sobi, Inc. at (866) 773-5274 and www.VONJO.com or FDA at 1-800-FDA-1088 or www.fda.gov/medwatch.

7 DRUG INTERACTIONS

Co-administration of VONJO with moderate CYP3A4 inhibitors can increase the exposure to pacritinib. Monitor for increased adverse reactions of VONJO when administered with moderate CYP3A4 inhibitors (7.1).

VONJO is an inhibitor of P-gp, BCRP, and CYP1A2 and an inducer of CYP3A4 and CYP2C19. Monitor patients concomitantly receiving substrates of these transporters and enzymes, and adjust dose of the substrates as needed (7.2).

VONJO may reduce the effectiveness of hormonal contraceptives (7.2)

8 USE IN SPECIFIC POPULATIONS

Lactation: Advise not to breastfeed (8.2).

Hepatic Impairment: For patients with severe hepatic impairment (Child-Pugh C), the recommended dosage is 100 mg twice daily (8.6).

Renal Impairment: Avoid use in patients with eGFR <30 mL/min (8.7).

FULL PRESCRIBING INFORMATION

RECENT MAJOR CHANGES

Warnings and Precautions (5.9) 11/2024

1 INDICATIONS AND USAGE

VONJO is indicated for the treatment of adults with intermediate or high-risk primary or secondary (post-polycythemia vera or post-essential thrombocythemia) myelofibrosis (MF) with a platelet count below 50 × 10^9/L.

This indication is approved under accelerated approval based on spleen volume reduction [see Clinical Studies (14.2)]. Continued approval for this indication may be contingent upon verification and description of clinical benefit in a confirmatory trial(s).

2 DOSAGE AND ADMINISTRATION

2.1 Recommended Dosage

The recommended dosage of VONJO is 200 mg orally twice daily. VONJO may be taken with or without food.

Swallow capsules whole. Do not open, break, or chew capsules.

Patients who are on treatment with other kinase inhibitors before the initiation of VONJO must taper or discontinue according to the prescribing information for that drug.

2.2 Monitoring for Safety

Perform a complete blood count (CBC; including white blood cell count differential and platelet count), coagulation testing (prothrombin time, partial thromboplastin time, thrombin time, and international normalized ratio) and a baseline electrocardiogram (ECG), prior to starting VONJO, and monitor as clinically indicated while the patient is on treatment.

2.3 Missed Dose

If a dose of VONJO is missed, the patient should take the next prescribed dose at its scheduled time. Extra capsules should not be taken to make up for the missed dose.

2.4 Dose Interruption for Planned Surgical Procedures or Other Interventions

Discontinue VONJO 7 days prior to elective surgery or invasive procedures because of the risk of hemorrhage and restart only after hemostasis is assured.

2.5 Dose Modification for Adverse Reactions

Dose modifications for diarrhea, thrombocytopenia, hemorrhage, and prolonged QT interval are described in Table 1, Table 2, Table 3, and Table 4 respectively. See Warning and Precautions (5.1, 5.2, 5.3, and 5.4) for additional risk minimization recommendations.

Dose levels for VONJO are as follows: 200 mg twice daily (initial starting dose), 100 mg twice daily (first dose reduction), 100 mg once daily (second dose reduction). Discontinue VONJO in patients unable to tolerate a dose of 100 mg daily.

Table 1 Dosage Modification for Diarrhea

Toxicity | Management/Action
New onset of diarrhea | - Initiate anti-diarrheal medications. - Encourage adequate oral hydration.
Grade 3 or 4 a | - Hold VONJO until the diarrhea resolves to Grade 1b or lower or baseline. Restart VONJO at the last given dose. - Intensify anti-diarrheal regimen. Provide fluid replacement. - If diarrhea recurs, hold VONJO until the diarrhea resolves to Grade 1b or lower or baseline. Restart VONJO at 50% of the last given dose once the toxicity has resolved. - Concomitant antidiarrheal treatment is required for patients restarting VONJO.
aIncrease of at least 7 stools per day over baseline, or hospitalization indicated, or severe increase in ostomy output over baseline, or if limiting self-care.
bIncrease of <4 stools per day over baseline or mild increase in ostomy output compared to baseline.

Table 2 Dose Modification for Thrombocytopenia

Worsening Thrombocytopenia | Action
For clinically significant worsening of thrombocytopenia that lasts more than 7 days | - Hold VONJO. Restart VONJO at 50% of the last given dose once the toxicity has resolved. - If toxicity recurs hold VONJO. Restart VONJO at 50% of the last given dose once the toxicity has resolved.

Table 3 Dose Modification for Hemorrhage

Toxicity | Action
Moderate bleeding; intervention indicated | - Hold VONJO until hemorrhage resolves. Restart VONJO at the last given dose. - If hemorrhage recurs, hold VONJO until resolution then restart at 50% of the last given dose.
Severe bleeding; transfusion, invasive intervention, or hospitalization indicated | - Hold VONJO until hemorrhage resolves. - Restart VONJO at 50% of the last given dose. - If bleeding recurs, discontinue VONJO.
Life-threatening bleeding; urgent intervention indicated. | - Discontinue VONJO.

Table 4 Dose Modification for Prolonged QT Interval

Toxicity | Action
QTc prolongation >500 msec or >60 msec from baseline | - Hold VONJO. - If QTc prolongation resolves to ≤480 msec or baseline within 1 week, restart VONJO at the same dose. - If time to resolution is greater than 1 week, restart VONJO at a reduced dose.

2.6 Dosage Modification for Patients with Severe Hepatic Impairment

The recommended dosage of VONJO in patients with severe hepatic impairment [Child-Pugh C] is 100 mg twice daily. Dosage may be increased to 200 mg twice daily if the treatment is not effective after 12 weeks and there are no safety concerns; continue monitoring for safety [see Use in Specific Populations (8.6) and Clinical Pharmacology (12.3)].

3 DOSAGE FORMS AND STRENGTHS

Capsule: 100 mg, oblong, size 0 hard gelatin capsule with an opaque scarlet cap printed with “Pacritinib 100 mg” and opaque gray body printed with “C78837”.

4 CONTRAINDICATIONS

VONJO is contraindicated in patients concomitantly using strong CYP3A4 inhibitors or inducers as these medications can significantly alter exposure to pacritinib, which may increase the risk of adverse reactions or impair efficacy [see Warnings and Precautions (5.1, 5.2, 5.3, 5.4), Drug Interactions (7.1), and Clinical Pharmacology (12.3)].

5 WARNINGS AND PRECAUTIONS

5.1 Hemorrhage

Serious (11%) and fatal (2%) hemorrhages have occurred in VONJO-treated patients with platelet counts <100 x 10 ^9/L. Serious (13%) and fatal (2%) hemorrhages have occurred in VONJO-treated patients with platelet counts <50 x 10 ^9/L. Grade ≥3 bleeding events (defined as requiring transfusion or invasive intervention) occurred in 15% of patients treated with VONJO compared to 7% of patients treated on the control arm. Due to hemorrhage, VONJO dose-reductions, dose interruptions, or permanent discontinuations occurred in 3%, 3%, and 5% of patients, respectively.

Avoid use of VONJO in patients with active bleeding and hold VONJO 7 days prior to any planned surgical or invasive procedures.

Assess platelet counts periodically, as clinically indicated [see Warnings and Precautions (5.3)] . Manage hemorrhage using treatment interruption and medical intervention [see Dosage and Administration (2.5)] .

5.2 Diarrhea

VONJO caused diarrhea in approximately 48% of patients compared to 15% of patients treated on the control arm in a clinical trial. The median time to resolution in VONJO-treated patients was 2 weeks. The incidence of reported diarrhea decreased over time with 41% of patients reporting diarrhea in the first 8 weeks of treatment, 15% in Weeks 8 through 16, and 8% in Weeks 16 through 24. Diarrhea resulted in treatment interruption in 3% of VONJO-treated patients. Serious diarrhea adverse reactions occurred in 2% of patients treated with VONJO compared to no such adverse reactions in patients in the control arm. In postmarketing reports, severe diarrhea leading to acute kidney injury and treatment discontinuation has been reported with VONJO.

Control pre-existing diarrhea before starting VONJO treatment. Manage diarrhea with antidiarrheal medications, fluid replacement, and dose-modification. Upon initiation of therapy, prescribe an anti-diarrheal medication (e.g., loperamide), and instruct patients to treat diarrhea promptly at the first onset of symptoms (change in frequency or consistency of bowel movements) after starting VONJO. Interrupt or reduce VONJO dose in patients with significant diarrhea despite optimal supportive care [see Dosage and Administration (2.5)].

5.3 Thrombocytopenia

VONJO can cause worsening thrombocytopenia. VONJO dosing was reduced due to worsening thrombocytopenia in 2% of patients with pre-existing moderate to severe thrombocytopenia (platelet count <100 x 10 ^9/L). VONJO dosing was reduced due to worsening thrombocytopenia in 2% of patients with pre-existing severe thrombocytopenia (platelet count <50 x 10 ^9/L).

Monitor platelet count prior to VONJO treatment and as clinically indicated during treatment [see Dosage and Administration (2.2)]. Interrupt VONJO in patients with clinically significant worsening of thrombocytopenia that lasts for more than 7 days. Restart VONJO at 50% of the last given dose once the toxicity has resolved. If toxicity recurs hold VONJO. Restart VONJO at 50% of the last given dose once the toxicity has resolved [see Dosage and Administration (2.5)].

5.4 Prolonged QT Interval

VONJO can cause prolongation of the QTc interval. QTc prolongation of >500 msec was higher in VONJO-treated patients than in patients in the control arm (1.4% vs 1%). QTc increase from baseline by 60 msec or higher was greater in VONJO-treated patients than in control arm patients (1.9% vs 1%). Adverse reactions of QTc prolongation were reported for 3.8% of VONJO-treated patients and 2% of control arm patients. No cases of torsades de pointes were reported.

Avoid use of VONJO in patients with a baseline QTc of >480 msec. Avoid use of drugs with significant potential for QTc prolongation in combination with VONJO. Correct hypokalemia prior to and during VONJO treatment.

Manage QTc prolongation using VONJO interruption and electrolyte management [see Dosage and Administration (2.5)] .

5.5 Major Adverse Cardiac Events (MACE)

Another Janus associated kinase (JAK)-inhibitor has increased the risk of MACE, including cardiovascular death, myocardial infarction, and stroke (compared to those treated with TNF blockers) in patients with rheumatoid arthritis, a condition for which VONJO is not indicated.

Consider the benefits and risks for the individual patient prior to initiating or continuing therapy with VONJO particularly in patients who are current or past smokers and patients with other cardiovascular risk factors. Patients should be informed about the symptoms of serious cardiovascular events and the steps to take if they occur.

5.6 Thrombosis

Another JAK-inhibitor has increased the risk of thrombosis, including deep venous thrombosis, pulmonary embolism, and arterial thrombosis (compared to those treated with TNF blockers) in patients with rheumatoid arthritis, a condition for which VONJO is not indicated.

Patients with symptoms of thrombosis should be promptly evaluated and treated appropriately.

5.7 Secondary Malignancies

Another JAK-inhibitor has increased the risk of lymphoma and other malignancies excluding non-melanoma skin cancer (NMSC) (compared to those treated with TNF blockers) in patients with rheumatoid arthritis, a condition for which VONJO is not indicated. Patients who are current or past smokers are at additional increased risk.

Consider the benefits and risks for the individual patient prior to initiating or continuing therapy with VONJO, particularly in patients with a known malignancy (other than a successfully treated NMSC), patients who develop a malignancy, and patients who are current or past smokers.

5.8 Risk of Infection

Another JAK-inhibitor increased the risk of serious infections (compared to best available therapy) in patients with myeloproliferative neoplasms. Serious bacterial, mycobacterial, fungal and viral infections may occur in patients treated with VONJO. Delay starting therapy with VONJO until active serious infections have resolved. Observe patients receiving VONJO for signs and symptoms of infection and manage promptly. Use active surveillance and prophylactic antibiotics according to clinical guidelines.

5.9 Interactions With CYP3A4 Inhibitors or Inducers

Co-administration of VONJO with strong CYP3A4 inhibitors or inducers is contraindicated. Monitor for increased adverse reactions of VONJO when administered with moderate CYP3A4 inhibitors [see Contraindications (4), Drug Interactions (7.1), and Clinical Pharmacology (12.3)].

6 ADVERSE REACTIONS

The following clinically significant adverse reactions are described elsewhere in the labeling:

- Hemorrhage [see Warnings and Precautions (5.1)]
- Diarrhea [see Warnings and Precautions (5.2)]
- Thrombocytopenia [see Warnings and Precautions (5.3)]
- Prolonged QT Interval [see Warnings and Precautions (5.4)]
- Major Adverse Cardiac Events [see Warnings and Precautions (5.5)]
- Thrombosis [see Warnings and Precautions (5.6)]
- Secondary Malignancies [see Warnings and Precautions (5.7)]
- Risk of Infection [see Warnings and Precautions (5.8)]

6.1 Clinical Trials Experience

Because clinical trials are conducted under widely varying conditions, adverse reaction rates observed in the clinical trials of a drug cannot be directly compared to rates in the clinical trials of another drug and may not reflect the rates observed in practice.

PERSIST-2 Trial

The safety of VONJO was evaluated in the randomized, controlled PERSIST-2 trial [see Clinical Studies (14)] . In PERSIST-2, key eligibility criteria included adults with intermediate or high-risk primary or secondary (post-polycythemia vera or post-essential thrombocythemia) MF with splenomegaly and a platelet count ≤100 × 10 ^9/L. Prior Janus associated kinase (JAK) inhibitor therapy was permitted. Patients received VONJO at 200 mg twice daily (n=106), 400 mg once daily (n=104), or best available therapy (BAT) (n=98). Forty-seven (44%) of the 106 patients treated with VONJO 200 mg twice daily had a baseline platelet count of <50 × 10 ^9/L. The 400 mg once daily dose could not be established to be safe, so further information on this arm is not provided.

In PERSIST-2, among the 106 patients treated with VONJO 200 mg twice daily, the median baseline hemoglobin was 9.7 g/dL and the median drug exposure was 25 weeks. Fifty-four percent of patients were exposed for 6 months, and 18% were exposed for approximately 12 months. Accounting for dose reductions, the average daily dose (mean relative dose intensity) and median daily dose (median relative dose intensity) were 380 mg (95%) and 400 mg (100%), respectively, for patients receiving VONJO twice daily.

The median age of patients who received VONJO 200 mg twice daily was 67 years (range: 39 to 85 years), 59% were male, 86% were White, 3% were Asian, 2% were Native Hawaiian or Other Pacific Islander, 0% were Black, 9% did not report race, and 87% had an Eastern Cooperative Oncology Group performance status of 0 to 1.

Serious adverse reactions occurred in 47% of patients treated with VONJO 200 mg twice daily and in 31% of patients treated with BAT. The most frequent serious adverse reactions occurring in ≥3% patients receiving VONJO 200 mg twice daily were anemia (8%), thrombocytopenia (6%), pneumonia (6%), cardiac failure (4%), disease progression (3%), pyrexia (3%), and squamous cell carcinoma of skin (3%). Fatal adverse reactions occurred in 8% of patients receiving VONJO 200 mg twice daily and in 9% of patients treated with BAT. The fatal adverse reactions among patients treated with VONJO 200 mg twice daily included events of disease progression (3%), and multiorgan failure, cerebral hemorrhage, meningorrhagia, and acute myeloid leukemia in <1% of patients each, respectively.

Permanent discontinuation due to an adverse reaction occurred in 15% of patients receiving VONJO 200 mg twice daily compared to 12% of patients treated with BAT. The most frequent reasons for permanent discontinuation in ≥2% of patients receiving VONJO 200 mg twice daily included anemia (3%) and thrombocytopenia (2%).

Drug interruptions due to an adverse reaction occurred in 27% of patients who received VONJO 200 mg twice daily compared to 10% of patients treated with BAT. The most frequent reasons for drug interruption in ≥2% of patients receiving VONJO 200 mg twice daily were anemia (5%), thrombocytopenia (4%), diarrhea (3%), nausea (3%), cardiac failure (3%), neutropenia (2%), and pneumonia (2%).

Dosage reductions due to an adverse reaction occurred in 12% of patients who received VONJO 200 mg twice daily compared to 7% of patients treated with BAT. Adverse reactions requiring dosage reduction in ≥2% of patients who received VONJO 200 mg twice daily included thrombocytopenia (2%), neutropenia (2%), conjunctival hemorrhage (2%), and epistaxis (2%).

The most common adverse reactions in ≥20% of patients (N=106) were diarrhea, thrombocytopenia, nausea, anemia, and peripheral edema.

Table 5 summarizes the common adverse reactions in PERSIST-2 during randomized treatment.

Table 5 Adverse Reactions Reported in ≥10% Patients Receiving VONJO 200 mg Twice Daily or Best Available Therapy During Randomized Treatment in PERSIST-2

Adverse Reactions | VONJO (200 mg Twice Daily) (N=106) |  | Best Available Therapy (N=98)
Adverse Reactions | All Gradesa % | Grade ≥3 % | All Gradesa % | Grade ≥3 %
Diarrhea | 48 | 4 | 15 | 0
Thrombocytopenia | 34 | 32 | 23 | 18
Nausea | 32 | 1 | 11 | 1
Anemia | 24 | 22 | 15 | 14
Peripheral edema | 20 | 1 | 15 | 0
Vomiting | 19 | 0 | 5 | 1
Dizziness | 15 | 1 | 5 | 0
Pyrexia | 15 | 1 | 3 | 0
Epistaxis | 12 | 5 | 13 | 1
Dyspnea | 10 | 0 | 9 | 3
Pruritus | 10 | 2 | 6 | 0
Upper respiratory tract infection | 10 | 0 | 6 | 0
Cough | 8 | 2 | 10 | 0
aGrade by CTCAE Version 4.03

6.2 Postmarketing Experience

The following adverse reactions have been identified during post-approval use of VONJO. Because these reactions are reported voluntarily from a population of uncertain size, it is not always possible to reliably estimate their frequency or establish a causal relationship to drug exposure:

- Renal: Acute or subacute kidney injury (secondary to diarrhea) [see Warnings and Precautions (5.2)]

7 DRUG INTERACTIONS

7.1 Effect of Other Drugs on VONJO

Strong and Moderate CYP3A4 Inhibitors

Pacritinib is predominantly metabolized by CYP3A4. Concomitant use of VONJO with strong and moderate CYP3A4 inhibitors increases pacritinib exposure, which may increase the risk of exposure-related adverse reactions [see Clinical Pharmacology (12.3)]

Co-administration of VONJO with strong CYP3A4 inhibitors is contraindicated [see Contraindications (4)].

Monitor patients concomitantly receiving moderate CYP3A4 inhibitors (e.g., fluconazole) for increased adverse reactions and consider VONJO dose modifications based on safety [see Dose Modifications for Adverse Reactions (2.5)]. Concomitant use of VONJO with doses of fluconazole greater than 200 mg once daily has not been studied.

Strong CYP3A4 Inducers

Pacritinib is predominantly metabolized by CYP3A4. Concomitant use of VONJO with strong CYP3A4 inducers decreases pacritinib exposure, which may reduce efficacy of VONJO [see Clinical Pharmacology (12.3)] .

Co-administration of VONJO with strong CYP3A4 inducers is contraindicated [see Contraindications (4)].

7.2 Effect of VONJO on Other Drugs

CYP1A2 Substrates

Pacritinib is an inhibitor of CYP1A2. VONJO increases the plasma concentrations of CYP1A2 substrates [see Clinical Pharmacology (12.3)] ,which may increase the risk of adverse reactions from the CYP1A2 substrate.

Monitor for CYP1A2 substrate related adverse reactions more frequently, unless otherwise recommended in the substrate Prescribing Information, when VONJO is used concomitantly with CYP1A2 substrates where minimal substrate concentration changes may lead to serious adverse reactions.

CYP2C19 Substrates

Pacritinib is an inducer of CYP2C19. VONJO decreases the plasma concentrations of CYP2C19 substrates [see Clinical Pharmacology (12.3)] , which may decrease the efficacy from the CYP2C19 substrate.

Monitor the efficacy of CYP2C19 substrate more frequently, unless otherwise recommended in the substrate Prescribing Information, when VONJO is used concomitantly with CYP2C19 substrates where minimal substrate concentration changes may lead to diminished efficacy. Dose adjustment of CYP2C19 substrates may be needed.

CYP3A4 Substrates

Pacritinib is an inducer of CYP3A4. VONJO decreases the plasma concentrations of CYP3A4 substrates [see Clinical Pharmacology (12.3)] , which may decrease the efficacy from the CYP3A4 substrate.

Monitor the efficacy of CYP3A4 substrate more frequently, unless otherwise recommended in the substrate Prescribing Information, when VONJO is used concomitantly with CYP3A4 substrates where minimal substrate concentration changes may lead to diminished efficacy. Dose adjustment of CYP3A4 substrates may be needed.

Hormonal Contraceptives

Avoid concomitant use of VONJO with hormonal contraceptives except for intrauterine systems containing levonorgestrel. The effectiveness of hormonal contraceptives, except for intrauterine systems containing levonorgestrel, may be reduced when used with VONJO.

If contraception is needed or desired, an alternate contraceptive that is not affected by CYP3A4 inducers (e.g., an intrauterine system) or additional nonhormonal contraceptive (e.g., condoms) should be used when treated concomitantly with VONJO, and for 30 days after last dose of VONJO.

P-gp Substrates

Pacritinib is an inhibitor of P-gp. VONJO increases the plasma concentrations of P-gp substrates [see Clinical Pharmacology (12.3)] , which may increase the risk of adverse reactions from the P-gp substrate.

Monitor for P-gp substrate related adverse reactions more frequently, unless otherwise recommended in the substrate Prescribing Information, when VONJO is used concomitantly with P-gp substrates where minimal substrate concentration changes may lead to serious adverse reactions.

Digoxin: Measure serum digoxin concentrations before initiating concomitant use with VONJO and continue monitoring serum digoxin concentrations as recommended in the Prescribing Information for digoxin [see Clinical Pharmacology (12.3)] .

BCRP substrates

Pacritinib is an inhibitor of BCRP. VONJO increases the plasma concentrations of BCRP substrates [see Clinical Pharmacology (12.3)] , which may increase the risk of adverse reactions from the BCRP substrate.

When used concomitantly with VONJO, monitor for BCRP substrate related adverse reactions more frequently and consider dose reduction of the BCRP substrate according to its Prescribing Information.

Rosuvastatin: The dose of rosuvastatin should not exceed 20 mg once daily when concomitantly used with VONJO [see Clinical Pharmacology (12.3)] .

8 USE IN SPECIFIC POPULATIONS

8.1 Pregnancy

Risk Summary

There are no available data on VONJO use in pregnant women to evaluate for a drug-associated risk of major birth defects, miscarriage, or adverse maternal or fetal outcomes. In animal reproduction studies, administration of pacritinib to pregnant mice or rabbits at exposures that were considerably lower than those observed at the recommended human dose were associated with maternal toxicity and embryonic and fetal loss (see Data) . Advise pregnant women of the potential risk to a fetus. Consider the benefits and risks of VONJO for the mother and possible risks to the fetus when prescribing VONJO to a pregnant woman.

The estimated background risk of major birth defects and miscarriage for the indicated population(s) is unknown. All pregnancies have a background risk of birth defect, loss, or other adverse outcomes. In the U.S. general population, the estimated background risk of major birth defects and miscarriage in clinically recognized pregnancies is 2% to 4% and 15% to 20%, respectively.

Data

Animal Data

Pacritinib was administered orally to pregnant mice at doses of 30, 100, or 250 mg/kg/day from gestation day 6 to gestation day 15. Pacritinib was also administered orally to pregnant rabbits at doses of 15, 30, or 60 mg/kg/day from gestation day 7 until gestation day 20. In both species, pacritinib was associated with maternal toxicity, which resulted in post-implantation loss in mice, abortions in rabbits, and reduced fetal body weights in mice and rabbits at exposures 0.1 times (mice) and 0.3 times (rabbits) the exposure at the recommended human dose (AUC-based). In mice, the high dose was associated with an increased incidence of an external malformation (cleft palate) in the presence of maternal toxicity.

In a pre- and post-natal development study in mice, pregnant animals were dosed with pacritinib from implantation through lactation at 30, 100, or 250 mg/kg/day. Maternal toxicity was noted at 250 mg/kg and associated with increased gestation length and dystocia, lowered mean birth weights and neonatal survival, and transiently delayed startle response, learning, and memory development at weaning.

8.2 Lactation

Risk Summary

There are no data on the presence of pacritinib in either human or animal milk, the effects on the breastfed child, or the effects on milk production. It is not known whether VONJO is excreted in human milk. Because of the potential for serious adverse reactions in the breastfed child, advise patients that breastfeeding is not recommended during treatment with VONJO, and for 2 weeks after the last dose.

8.3 Females and Males of Reproductive Potential

Infertility

Males

Pacritinib reduced male mating and fertility indices in BALB/c mice [see Nonclinical Toxicology (13.1)]. Pacritinib may impair male fertility in humans.

8.4 Pediatric Use

Safety and effectiveness in pediatric patients have not been established.

8.5 Geriatric Use

Clinical studies of VONJO did not include sufficient numbers of subjects aged 65 years and over to determine whether they respond differently from younger subjects.

8.6 Hepatic Impairment

In patients with severe hepatic impairment [Child-Pugh C], the recommended dosage of VONJO is 100 mg twice daily. Dosage may be increased to 200 mg twice daily if the treatment is not effective after 12 weeks and there are no safety concerns. Monitor hepatically-impaired patients for adverse reactions and consider VONJO dose modifications based on safety and efficacy [see Dosage and Administration (2.5), Clinical Pharmacology (12.3)].

No dose modification is recommended for patients with mild [Child-Pugh A] or moderate [Child-Pugh B] hepatic impairment [see Clinical Pharmacology (12.3)].

8.7 Renal Impairment

Administration of a single dose of VONJO 400 mg to subjects with renal impairment resulted in approximately 30% increase in C maxand AUC of pacritinib in subjects with eGFR 15 to 29 mL/min and eGFR <15 mL/min on hemodialysis compared to subjects with normal renal function (eGFR ≥90 mL/min). Avoid use of VONJO in patients with eGFR <30 mL/min [see Clinical Pharmacology (12.3)].

10 OVERDOSAGE

Overdosage may lead to gastrointestinal toxicities, myelosuppression, blurred vision, dizziness, worsening performance status, and sepsis. There is no known antidote for overdose with VONJO. Hemodialysis is not expected to enhance the elimination of VONJO.

11 DESCRIPTION

VONJO contains pacritinib citrate, a kinase inhibitor with the chemical name (2E,16E)-11-[2-(pyrrolidin-1-yl)ethoxy]-14,19-dioxa-5,7,27-triazatetracyclo[19.3.1.1(2,6).1(8,12)]heptacosa-1(25),2,4,6,8,10,12(26),16,21,23-decaene citrate and a molecular weight of 664.7 as citrate salt and 472.59 as a free base. The molecular formula is C28H32N4O3•C6H8O7 and the structural formula is:

VONJO capsule is for oral administration. Each capsule contains 100 mg of pacritinib equivalent to 140.65 mg of pacritinib citrate and the inactive ingredients are microcrystalline cellulose NF, polyethylene glycol 8000 (PEG 8000) NF, and magnesium stearate NF. The gelatin capsule is bovine derived. The capsule shell contains gelatin, titanium dioxide, black iron oxide, erythrosine, red iron oxide, and printing ink containing shellac, propylene glycol, titanium dioxide, sodium hydroxide, and povidone.

12 CLINICAL PHARMACOLOGY

12.1 Mechanism of Action

Pacritinib is an oral kinase inhibitor with activity against wild type Janus associated kinase 2 (JAK2), mutant JAK2V617F, FMS-like tyrosine kinase 3 (FLT3), and interleukin 1 receptor associated kinase-1 (IRAK1) which contribute to signaling of a number of cytokines and growth factors that are important for hematopoiesis and immune function. Pacritinib is also an inhibitor of activin A receptor, type 1/activin receptor like-kinase 2 (ACVR1/ALK2).

MF is often associated with dysregulated JAK2 signaling. At clinically relevant concentrations, pacritinib does not inhibit JAK1. Pacritinib has higher inhibitory activity for JAK2 compared to JAK3 and tyrosine kinase 2 (TYK2). Pacritinib exhibits inhibitory activity against additional cellular kinases, such as colony stimulating factor 1 receptor (CSF1R), of which the clinical relevance in myelofibrosis is unknown.

12.2 Pharmacodynamics

Pacritinib inhibited the phosphorylation of signal transducer and activator of transcription 5 (STAT5) protein in a dose-dependent manner (ex vivo) in expanded erythroid progenitor cells derived from healthy subjects. Administration of single doses of 400 mg pacritinib resulted in modest inhibition of interleukin-6-induced STAT3 phosphorylation in whole blood derived from healthy subjects.

Cardiac Electrophysiology

In a 24-week study of 54 patients with MF treated with VONJO 200 mg twice daily, the maximum mean (90% confidence interval) change in QTcF from baseline was 11 (90% CI: 5-17) msec.

12.3 Pharmacokinetics

Pacritinib steady-state mean (CV%) Cmax is 8.4 mg/L (32.4%) and AUC0-12 is 95.6 mg×h/L (33.1%) following administration of VONJO 200 mg twice daily in patients with MF. Pharmacokinetics of pacritinib increases in a less than dose-proportional manner. VONJO 200 mg twice daily accumulates 386% and reaches steady-state within a week.

Absorption

Pacritinib achieves Cmax within approximately 4 to 5 hours post-dose.

Effect of Food

There was no significant effect of food on the pharmacokinetics of pacritinib following oral administration of VONJO 200 mg with a high-fat meal.

Distribution

The median (range) apparent volume of distribution of pacritinib at steady state is 229 L (156 to 591 L) in patients with MF taking 200 mg twice daily. Plasma protein binding of pacritinib is approximately 98.8%.

Metabolism

Pacritinib is predominantly metabolized by the CYP3A4 isozyme. Pacritinib is the major circulating component and the pharmacologic activity is mainly attributed to the parent molecule. Two major metabolites, M1 and M2, in human whole plasma represent 9.6% and 10.5% of parent drug exposure, respectively.

Elimination

The mean apparent clearance at steady-state (CV%) of pacritinib is 2.09 L/h (33.1%), and mean effective half-life (CV%) is 27.7 hours (17.0%).

Excretion

Following a single oral administration of radiolabeled pacritinib 400 mg in healthy adult subjects, 87% of the radioactivity was recovered in feces, and 6% was recovered in urine. No unchanged drug was excreted in feces and 0.12% of unchanged drug was excreted in urine.

Specific Populations

No clinically significant differences in the pharmacokinetics of pacritinib were observed based on age, sex, body weight, or race.

Patients With Renal Impairment

Pacritinib Cmax and AUC were similar in subjects with eGFR 30 to 89 mL/min, as estimated by the MDRD study equation, compared to subjects with eGFR ≥90 mL/min. The Cmax and AUC increased approximately 30% in subjects with eGFR 15 to 29 mL/min and eGFR <15 mL/min on hemodialysis.

Patients With Hepatic Impairment

The effect of hepatic impairment on the pharmacokinetics of pacritinib was studied in subjects with normal or impaired hepatic function at 200 mg VONJO twice daily for 14 days. The geometric mean AUC of total pacritinib decreased in subjects with moderate [Child-Pugh B, n=8] or severe hepatic impairment [Child-Pugh C, n=6] compared to subjects with normal hepatic function (n=11) due to reduced plasma protein binding. The geometric mean AUC of unbound pacritinib, the pharmacologically relevant parameter, was similar in healthy subjects compared to subjects with moderate hepatic impairment and increased by 23% in subjects with severe hepatic impairment (see Table 6).

Table 6 Steady-State Pharmacokinetic Changes in Pacritinib at 200 mg VONJO BID: Subjects with Moderate / Severe Hepatic Impairment vs. Normal Hepatic Function

Hepatic impairment | Ratio (90% CI) of pacritinib exposure^1
Hepatic impairment | Unbound Cmax | Unbound AUC0-tau
Moderate impairment (Child-Pugh B) | 1.06; (0.72, 1.58) | 1.05; (0.69, 1.60)
Severe impairment (Child-Pugh C) | 1.24; (0.93, 1.65) | 1.23; (0.91, 1.66)

Notes: AUC0-tau = Area under the curve from zero to tau post-dose after 14 days twice daily dosing with VONJO 200 mg; CI = Confidence Interval; Cmax = Maximum plasma concentration.

^1Ratios for Cmax and AUC compare exposure of unbound pacritinib in subjects with hepatic impairment vs normal hepatic function following administration of VONJO 200 mg BID for 14 days.

Drug Interactions

Effects of Other Drugs on the Pharmacokinetics of VONJO

The effect of co-administered drugs on the exposure of pacritinib is shown in Table 7 and Table 8.

Table 7 Change in Pharmacokinetics of Pacritinib Following Administration of a Single 400 mg Dose VONJO in the Presence of Co-administered Drugs

Co-administered Drug | Regimen of Co-administered Drug | Ratio (90% CI) of pacritinib exposure ^1
Co-administered Drug | Regimen of Co-administered Drug | Cmax | AUC 0-t
Clarithromycin (strong CYP3A4 inhibitor) | 500 mg every 12 hours for 5 days | 1.30; (1.22, 1.39) | 1.80; (1.67, 1.94)
Rifampin (strong CYP3A4 inducer) | 600 mg once daily for 10 days | 0.49; (0.43, 0.55) | 0.13; (0.11, 0.15)

Notes: AUC0-t = Area under the curve from zero to the last quantifiable concentration; CI = Confidence interval; CYP = Cytochrome P450
^1 Ratios for Cmax and AUC compare co-administration of the medication with VONJO vs. administration of single dose 400 mg VONJO alone

Table 8 Change in Pharmacokinetics of 200 mg VONJO BID at Steady State in the Presence of Co-administered Drugs

Co-administered Drug | Regimen of Co-administered Drug | Ratio (90% CI) of pacritinib exposure ^1
Co-administered Drug | Regimen of Co-administered Drug | C max | AUC 0-tau
Fluconazole (moderate CYP3A4 inhibitor) | 200 mg once daily for 7 days | 1.41; (1.35, 1.48) | 1.45; (1.39, 1.52)
Bosentan (moderate CYP3A4 inducer) | 125 mg twice daily for 7 days | 0.84; (0.76, 0.92) | 0.79; (0.72, 0.87)

Notes: AUC0-tau = Area under the curve for a dosing interval; BID = Twice daily; CI = Confidence interval; Cmax = Maximum plasma concentration; CYP = Cytochrome P450.
^1 Ratios for Cmax and AUC0-tau compare co-administration of the medication with 200 mg VONJO BID vs. administration of 200 mg VONJO alone at steady state.

Effects of VONJO on the Pharmacokinetics of Other Drugs

The effect of pacritinib on the exposure of other co-administered drugs is shown in Table 9.

Table 9 Change in Pharmacokinetics of Co-administered Drugs with 200 mg VONJO BID at Steady State

Co-administered Drug | Regimen of Co-administered Drug (single dose) | Ratio (90% CI) of exposure of co-administered drug ^1
Co-administered Drug | Regimen of Co-administered Drug (single dose) | C max | AUC
Caffeine (CYP1A2 substrate) | 100 mg | 0.99; (0.92, 1.07) | 1.22; (1.12, 1.32)
Midazolam (CYP3A4 substrate) | 2 mg | 0.40; (0.34, 0.46) | 0.40; (0.35, 0.46)
Omeprazole (CYP2C19 substrate) | 20 mg | 0.73; (0.46, 1.15) | 0.49; (0.27, 0.89)

Notes: AUC = Area under the curve from zero to the last quantifiable concentration displayed for caffeine and AUC from zero extrapolated to infinity displayed for midazolam and omeprazole; BID = Twice daily; CI = Confidence interval; Cmax = Maximum plasma concentration; CYP = Cytochrome P450.

^1 Ratios for Cmax and AUC compare a single dose of co-administered drug with 200 mg VONJO BID at steady state vs. administration of a single dose of the co-administered drug alone.

In Vitro Studies

Cytochrome P450 (CYP) Enzymes: Pacritinib is a time-dependent inhibitor of CYP1A2 and CYP3A4, and a reversible inhibitor of CYP3A4 and CYP2C19 (Ki ≤10 µM). Pacritinib shows less direct inhibition towards CYP1A2, CYP2B6, CYP2C8, CYP2C9, and CYP2D6 (Ki >10 µM). Pacritinib is an inducer of CYP1A2 and CYP3A4.

Transporter Systems

Table 10 Change in Pharmacokinetics of Co-administered Drugs with 200 mg VONJO BID at Steady State

Co-administered Drug | Regimen of Co-administered Drug (single dose) | Ratio (90% CI) of exposure of co-administered drug ^1
Co-administered Drug | Regimen of Co-administered Drug (single dose) | C max | AUC
Metformin (OCT1 substrate) | 500 mg | 0.96; (0.87, 1.07) | 1.05; (0.96, 1.15)
Digoxin (P-gp substrate) | 0.25 mg | 1.29; (1.13, 1.47) | 1.15; (1.05, 1.27)
Rosuvastatin (BCRP substrate) | 5 mg | 2.04; (1.79, 2.31) | 1.80; (1.63, 1.99)

Notes: AUC = Area under the curve from zero to the last quantifiable concentration displayed for digoxin and rosuvastatin and AUC from zero extrapolated to infinity displayed for metformin; BID = Twice daily; CI = Confidence interval; Cmax = Maximum plasma concentration; CYP = Cytochrome P450

^1 Ratios for Cmax and AUC compare a single dose of co-administered drug with 200 mg VONJO BID at steady state vs. administration of a single dose of the co-administered drug alone.

In Vitro Studies

Transporter Systems: Pacritinib is not a substrate of BCRP, MRP2, OAT1, OAT3, OATP1B1, OATP1B3, OCT1, OCT2, or P-gp. Pacritinib is an inhibitor of BCRP, OCT1, OCT2, and P-gp. Pacritinib is not an inhibitor of BSEP, MRP2, OAT1, or OAT3.

13 NONCLINICAL TOXICOLOGY

13.1 Carcinogenesis, Mutagenesis, and Impairment of Fertility

Pacritinib was not carcinogenic in the 6-month Tg.rasH2 transgenic mouse model. Pacritinib was not carcinogenic in a 2-year carcinogenicity study in rats at 0.004 times and 0.014 times, in males and females, respectively, the recommended human dose (AUC-based). Pacritinib exposures achieved in mice and rats during the carcinogenicity assessments were considerably lower than the exposure observed at the recommended human dose.

Pacritinib was not mutagenic in a bacterial mutagenicity assay (Ames test) or clastogenic in vitro in a chromosomal aberration assay (Chinese hamster ovary cells) or in vivo in a micronucleus test in mice.

In a fertility study in male BALB/c mice, pacritinib was administered for at least 70 days prior to cohabitation with untreated partners. Pacritinib had no effects at any dose level on uterine implantation, macroscopic findings, reproductive organ weights, and sperm evaluations. At 213.4 mg/kg/day (3.0 times, the recommended human dose, based on body surface area), reduced mating and fertility indices were observed in male BALB/c mice. In a fertility and early embryonic development study in CD-1 mice, no effects on male or female reproductive performance, including assessments of mating, fertility, estrous cyclicity, and intrauterine survival, were observed at doses up to 250 mg/kg/day (3.0 times, the recommended human dose, based on body surface area).

14 CLINICAL STUDIES

PERSIST-2

The efficacy of VONJO in the treatment of patients with intermediate or high-risk primary or secondary (post-polycythemia vera or post-essential thrombocythemia) MF was established in the PERSIST-2 trial.

PERSIST-2 enrolled patients with intermediate or high-risk primary or secondary (post-polycythemia vera or post-essential thrombocythemia) MF with splenomegaly and a platelet count ≤100 × 10^9/L. Both JAK2 naïve patients and patients with prior JAK2 inhibitor therapy were included. Patients were randomized 1:1:1 to receive VONJO 400 mg once daily, VONJO 200 mg twice daily, or best available therapy (BAT). BAT agents could be used alone, in combinations, sequentially, and intermittently, as clinically indicated by standards of care. BAT included any physician-selected treatment for MF and may have included ruxolitinib, hydroxyurea, glucocorticoids, erythropoietic agents, immunomodulatory agents, mercaptopurine, danazol, interferons, cytarabine, melphalan. BAT also included no treatment (“watch and wait”) or symptom-directed treatment without MF-specific treatment.

In this trial, 311 patients were randomized to receive VONJO 400 mg once daily (n=104), VONJO 200 mg twice daily (n=107), or BAT (n=100). The VONJO dose of 400 mg once daily was not established as safe and is not an approved dosage regimen.

The demographic characteristics of the efficacy population were median age of 68 years (range 32 to 91), 55% male, 86% Caucasian, and 14% non-Caucasian. The VONJO and BAT treatment arms were well balanced with respect to age, gender, race, ethnicity, body mass index, and geographic region. Sixty-eight percent of patients had primary MF, 20% had post-polycythemia vera MF, and 12% had post-essential thrombocythemia MF. Forty-six percent and 51% of patients in the VONJO and BAT treatment arms, respectively, had received prior ruxolitinib therapy. The median baseline hemoglobin level was 9.5 g/dL and 23% of patients were red blood cell (RBC) transfusion dependent at study entry. The median baseline platelet count was 55 × 10^9/L; 45% of patients had a platelet count <50 × 10^9/L. Patients had a baseline median spleen length of 14 cm assessed by magnetic resonance imaging (MRI) or computerized axial tomography (CAT).

Efficacy was established in patients who received VONJO 200 mg twice daily and had a platelet count <50 x 10^9 (N=31).

The most common agents used in the BAT treatment arm in patients with baseline platelet counts <50 × 10^9/L (N=32) were ruxolitinib (39%), watchful waiting (32%), and hydroxyurea (26%).

Spleen Volume Reduction

The efficacy of VONJO in the treatment of patients with primary or secondary MF was established based upon the proportion of patients in the efficacy population receiving VONJO 200 mg twice daily or BAT achieving ≥35% spleen volume reduction from baseline to Week 24 as measured by magnetic resonance imaging or computed tomography. Efficacy results for spleen volume reduction in patients with a platelet count <50 × 10^9/L are presented in Table 11

Table 11 Percentage of Patients Achieving ≥35% Reduction in Spleen Volume From Baseline to Week 24 in the Phase 3 Study, PERSIST-2 (Efficacy Population)

Patient Population | VONJO; 200mg Twice Daily; N=31 | Best Available Therapy; N=32
Baseline Platelets; <50 × 10^9/L | 9 (29.0%) | 1 (3.1%)
95% Confidence Interval (CI) | 14.2, 48.0 | 0.1, 16.2
Difference (VONJO-BAT) 95% CI | 25.9 (4.3,44.5)

A waterfall plot of the percentage of change in spleen volume from baseline to Week 24 is presented in Figure 1 for the PERSIST-2 patients with baseline platelet counts <50 × 10^9/L. The median reduction in spleen volume for patients with a platelet count <50 × 10^9/L was 27.3% for patients in the VONJO 200 mg twice daily group compared to 0.9% in the BAT group.

Figure 1 Waterfall Plot of Median Percent Change From Baseline in Spleen Volume at Week 24 in Patients With <50 × 10^9/L Platelet Counts in PERSIST-2a

a Dropout rates in VONJO and BAT arms were 26% and 44%, respectively.

16 HOW SUPPLIED/STORAGE AND HANDLING

16.1 How Supplied

VONJO is supplied in the following strength and package configuration:

Strength | NDC Number | Description | Capsules per Bottle
100 mg | 72482-100-12 | Hard, oblong, opaque, gelatin capsule with scarlet cap and gray body, printed with “Pacritinib 100 mg” on the cap and “C78837” on the body | 120

16.2 Storage

Store at room temperature, below 30°C (86°F). Keep the bottle tightly closed and protect from light. Store in original package. Dispense in original package or in a light-resistant container.

17 PATIENT COUNSELING INFORMATION

See FDA approved patient labeling (Patient Information).

Discuss the following with the patient prior to and during treatment with VONJO:

Current therapy with another kinase inhibitor

Advise patients who are currently taking a kinase inhibitor that they must taper or discontinue their current kinase inhibitor therapy according to the package insert for that drug prior to starting VONJO.

Hemorrhage

Advise patients that VONJO can cause hemorrhage and instruct them to consult their healthcare provider right away if bleeding occurs. Advise patients about how to recognize bleeding and of the urgent need to report any unusual bleeding to their physician. Patients should urgently seek emergency medical attention for any bleeding that cannot be stopped [see Warnings and Precautions (5.1)] .

Diarrhea

Advise patients that VONJO can cause diarrhea. Advise patients to stay hydrated while taking VONJO and to inform their physician if they experience diarrhea. Instruct patients to initiate antidiarrheal medication promptly at the first onset of symptoms (increase in frequency or change in consistency of bowel movements [loosening]) after starting VONJO. Advise patients to urgently seek emergency medical attention if diarrhea becomes severe [see Warnings and Precautions (5.2)].

Thrombocytopenia

Advise patients that VONJO can cause thrombocytopenia, and of the need to monitor complete blood counts before and during treatment [see Warnings and Precautions (5.3)].

Prolonged QT Interval

Advise patients to consult their healthcare provider immediately if they feel faint, lose consciousness, or have signs or symptoms suggestive of arrhythmia. Advise patients with a history of hypokalemia of the importance of monitoring their electrolytes [see Warnings and Precautions (5.4)].

Major Adverse Cardiac Events (MACE)

Advise patients that events of major adverse cardiac events (MACE) including myocardial infarction, stroke, and cardiovascular death, have been reported in clinical studies with another JAK-inhibitor used to treat rheumatoid arthritis, a condition for which VONJO is not indicated. Advise patients, especially current or past smokers or patients with other cardiovascular risk factors, to be alert for the development of signs and symptoms of cardiovascular events [see Warnings and Precautions (5.5)].

Thrombosis

Advise patients that events of deep vein thrombosis and pulmonary embolism have been reported in clinical studies with another JAK-inhibitor used to treat rheumatoid arthritis, a condition for which VONJO is not indicated. Advise patients to tell their healthcare provider if they develop any signs or symptoms of a DVT or PE [see Warnings and Precautions (5.6)].

Secondary Malignancies

Advise patients, especially current or past smokers and patients with a known secondary malignancy (other than a successfully treated NMSC), that lymphoma and other malignancies (excluding NMSC) have been reported in clinical studies with another JAK-inhibitor used to treat rheumatoid arthritis, a condition for which VONJO is not indicated [see Warnings and Precautions (5.7)].

Infections

Advise patients that treatment with another JAK-inhibitor has increased the risk of serious infections in patients with myeloproliferative neoplasms and that serious bacterial, mycobacterial, fungal and viral infections may occur in patients treated with VONJO. Inform patients of the signs and symptoms of infection and to report any such signs and symptoms promptly [see Warnings and Precautions (5.8)].

Nausea and Vomiting

Advise patients that nausea and vomiting may occur during treatment with VONJO. Instruct them on how to manage nausea and vomiting and to immediately inform their healthcare provider if nausea/vomiting become severe.

Drug–Drug Interactions

Advise patients to inform their healthcare providers of all medications they are taking, including prescription and over-the-counter medications, vitamins, herbal products, and dietary supplements [see Drug Interactions (7)].

Inform women of the possible reduced effectiveness of hormonal contraceptives when under treatment with VONJO and for 30 days after last dose. Advise women of childbearing potential receiving VONJO and hormonal contraception, to use additional nonhormonal contraception or use an alternative contraceptive that is not affected by CYP3A4 inducers [see Drug Interactions (7.2)].

Dosing

Advise patients to take VONJO twice a day, with or without food or drink. VONJO should be taken at similar times each day. Instruct patients to swallow the VONJO capsules whole and not to open, break, or chew the capsules [see Dosage and Administration (2.1)].

Instruct patients that if they miss a dose of VONJO, to skip the dose and take the next dose when it is due and return to the normal schedule [see Dosage and Administration (2.1)]. Warn patients not to take 2 doses to make up for the missed dose.

Instruct patients to discontinue VONJO 7 days prior to any surgery or invasive procedures (such as cardiac catheterization, coronary stenting or varicose vein ablation) due to the risk of bleeding and to only restart VONJO on the instruction of their healthcare provider.

Patients should not change or stop taking VONJO without first consulting their physician.

Lactation

Advise patients to avoid breastfeeding while taking VONJO and for 2 weeks after the final dose [see Use in Specific Populations (8.2)] .

Manufactured and marketed by:

Sobi, Inc.

77 4th Ave, FL 3 Waltham, MA, 02451

SOBI

VONJO® is a registered trademark of Sobi Inc. All rights reserved.

©2022 All rights reserved.

PATIENT INFORMATION VONJO (VON-joh) (pacritinib) capsules

What is VONJO?

VONJO is a prescription medicine used to treat adults with certain types of myelofibrosis who have a platelet count below 50 x 10 ^9/L.

It is not known if VONJO is safe and effective in children.

Before taking VONJO, tell your healthcare provider about all of your medical conditions, including if you:

- have active bleeding, have had severe bleeding, or plan to have surgery or invasive procedures. You should stop taking VONJO 7 days before any planned surgery or invasive procedures. See “What are the possible side effects of VONJO?”
- have diarrhea or commonly have loose stools
- have had a blood clot, heart attack, other heart problems, or stroke
- have a history of low blood levels of potassium. It is important that you get blood tests done during treatment with VONJO to monitor your body salts (electrolytes).
- smoke or were a smoker in the past
- have had any other cancers. See “What are the possible side effects of VONJO?”
- have an infection. See “What are the possible side effects of VONJO?”
- have nausea or vomiting
- have liver or kidney problems
- are pregnant or plan to become pregnant. It is not known if VONJO will harm your unborn baby
- are breastfeeding or plan to breastfeed. It is not known if VONJO passes into your breast milk. You should not breastfeed during treatment and for 2 weeks after your last dose of VONJO. Talk to your healthcare provider about the best way to feed your baby during this time.

Tell your healthcare provider about all the medicines you take,including prescription and over-the-counter medicines, vitamins, and herbal supplements. Taking VONJO with certain other medicines may affect the amount of VONJO or other medicines in your blood and may increase your risk of side effects or affect how well VONJO works.

Especially tell your healthcare provider if you take hormonal contraceptives (birth control). Hormonal birth control methods, except for intrauterine systems containing levonorgestrel may not work during treatment with VONJO and for 30 days after your last dose. Talk to your healthcare provider about birth control methods that may be right for you during treatment with VONJO.

Know the medicines you take. Keep a list of the medicines you take to show your healthcare provider and pharmacist when you get a new medicine.

How should I take VONJO?

- Take VONJO exactly as your healthcare provider tells you to take it.
- Do not change your dose or stop taking VONJO without first talking to your healthcare provider.
- If you take other kinase inhibitors, carefully follow your healthcare provider's instructions about how to slowly decrease (taper) your dose or stop the other kinase inhibitor medicines before you begin taking VONJO.
- VONJO is usually taken by mouth 2 times each day.
- Swallow VONJO capsules whole. Do not open, break, or chew capsules.
- You can take VONJO with or without food or drink.
- Take your VONJO doses at about the same time every day.
- If you notice any change in how often you have bowel movements, if they become softer or you have diarrhea, start taking an antidiarrheal medicine (for example, loperamide) as soon as you notice changes, as directed by your healthcare provider.
- If you miss a dose of VONJO, skip the dose and just take your next dose at your regularly scheduled time. Do not take 2 doses at the same time to make up for the missed dose.
- If you take too much VONJO, call your healthcare provider or go to the nearest emergency room right away and take your bottle of VONJO with you.

What are the possible side effects of VONJO?

VONJO can cause serious side effects including:

- Bleeding.VONJO can cause severe bleeding, which can be serious and, in some cases may lead to death.
- Stop taking VONJO and tell your healthcare provider right away if you develop any of these symptoms: unusual bleeding, bruising, and fever. Get medical help right away for any bleeding that you cannot stop.
- You will need to stop taking VONJO 7 days before any planned surgery or invasive procedure (such as a heart catheterization, stent placement in a coronary artery in your heart, or a procedure for varicose veins). Your healthcare provider should tell you when you can start taking VONJO again.
- Diarrhea.Diarrhea is common with VONJO, but can also be severe, and cause loss of too much body fluid (dehydration). Dehydration can lead to kidney problems. Tell your healthcare provider if you develop diarrhea during treatment with VONJO. Drink plenty of fluids to help prevent dehydration. Your healthcare provider will prescribe an anti-diarrheal medicine before you start VONJO. You should start taking the anti-diarrheal medicine right away if you get any symptoms of diarrhea, including any changes in consistency (such as loose stools) or increase in the number of daily bowel movements, during treatment with VONJO. Get emergency medical help right away if your diarrhea becomes severe.
- Worsening low platelet counts.
- Changes in the electrical activity of your heart called QTc prolongation. QTc prolongation can cause irregular heartbeats that can be life-threatening. Tell your healthcare provider right away if you feel dizzy, lightheaded, or faint.
- Increased risk of major cardiovascular events such as heart attack, stroke, or death in people have happened, especially in those who have cardiovascular risk factors and who are current or past smokers taking another Janus Kinase (JAK)-inhibitor to treat rheumatoid arthritis.

Get emergency help right away if you have any symptoms of a heart attack or stroke during treatment with VONJO, including:

- discomfort in the center of your chest that lasts for more than a few minutes, or that goes away and comes back
- severe tightness, pain, pressure, or heaviness in your chest, throat, neck, or jaw
- pain or discomfort in your arms, back, neck, jaw, or stomach
- shortness of breath with or without chest discomfort
- breaking out in a cold sweat
- nausea or vomiting
- feeling lightheaded
- weakness in one part or on one side of your body
- slurred speech

- Increased risk of blood clots.Blood clots in the veins of your legs (deep vein thrombosis, DVT) or lungs (pulmonary embolism, PE) have happened in some people taking another JAK-inhibitor for rheeumatoid arthritis and may be life-threatening.

Tell your healthcare provider right away if you have any signs and symptoms of blood clots during treatment with VONJO, including:

- swelling, pain, or tenderness in one or both legs
- sudden, unexplained chest pain
- shortness of breath or difficulty breathing
- Possible increased risk of new (secondary) cancers.People who take another JAK-inhibitor for rheumatoid arthritis have an increased risk of new (secondary) cancers, including lymphoma and other cancers, except non-melanoma skin cancer. The risk of new cancers is further increased in people who smoke or who smoked in the past.
- Risk of infection.People who have certain blood cancers and take another JAK-inhibitor have an increased risk of serious infections. People who take VONJO may also develop serious infections, including bacterial, mycobacterial, fungal, and viral infections. If you have a serious infection, your healthcare provider may not start you on VONJO until your infection is gone. Your healthcare provider will monitor you and treat you for any infections that you get during treatment with VONJO.

Tell your healthcare provider right away if you develop any of the following symptoms of infection:

- chills
- aches
- fever
- nausea
- vomiting
- weakness
- painful skin rash or blisters

The most common side effects of VONJO include:

- low platelet counts
- nausea and vomiting
- low red blood cell counts (anemia)
- swelling of your ankles, legs, and feet

Your healthcare provider will do blood tests and an electrocardiogram (ECG) before you start treatment with VONJO and as needed during treatment to check for side effects.

Your healthcare provider may change your dose or how often you take VONJO, temporarily stop or permanently stop treatment with VONJO if you have certain side effects.

VONJO may affect fertility in males. You may have problems fathering a child. Talk to your healthcare provider if this is a concern for you.

These are not all of the possible side effects with VONJO.

Call your doctor for medical advice about side effects. You may report side effects to FDA at 1-800-FDA-1088.

How should I store VONJO?

- Store VONJO at room temperature, below 86°F (30°C).
- Store VONJO in the original package.
- Keep the bottle tightly closed to protect VONJO from light.

Keep VONJO and all medicines out of the reach of children.

General information about the safe and effective use of VONJO.

Medicines are sometimes prescribed for purposes other than those listed in a Patient Information leaflet. Do not use VONJO for a condition for which it was not prescribed. Do not give VONJO to other people, even if they have the same symptoms that you have. It may harm them. You can ask your pharmacist or healthcare provider for information about VONJO that is written for health professionals.

What are the ingredients in VONJO?

Active ingredient: pacritinib

Inactive ingredients: microcrystalline cellulose, polyethylene glycol 8000 (PEG 8000), and magnesium stearate. The capsule shell contains gelatin, titanium dioxide, black iron oxide, erythrosine, red iron oxide, and printing ink containing shellac, propylene glycol, titanium dioxide, sodium hydroxide, and povidone.

Manufactured and Marketed by: Sobi Inc., 77 4th Ave, FL 3, Waltham, MA, 02451

VONJO® is a registered trademark of Sobi Inc. All rights reserved.

For more information call (866) 773-5274 or go to www.VONJO.com.

This Patient Information has been approved by the U.S. Food and Drug Administration. Revised: 10/2025

Principal Display Panel - 100 mg Carton Label

NDC 72482-100-12

Rx only

VONJO®

(pacritinib) capsules

100 mg

120 capsules

Swallow capsules whole.

Do not open, break, or chew capsules.

Keep out of the sight and reach of children.

Principal Display Panel - 100 mg Bottle Label

NDC 72482- 100-12

Rx only

VONJO®
(pacritinib) capsules

100 mg

120 capsules

Swallow capsules whole.

Do not open, break, or chew capsules.

Keep out of the sight and reach of children.